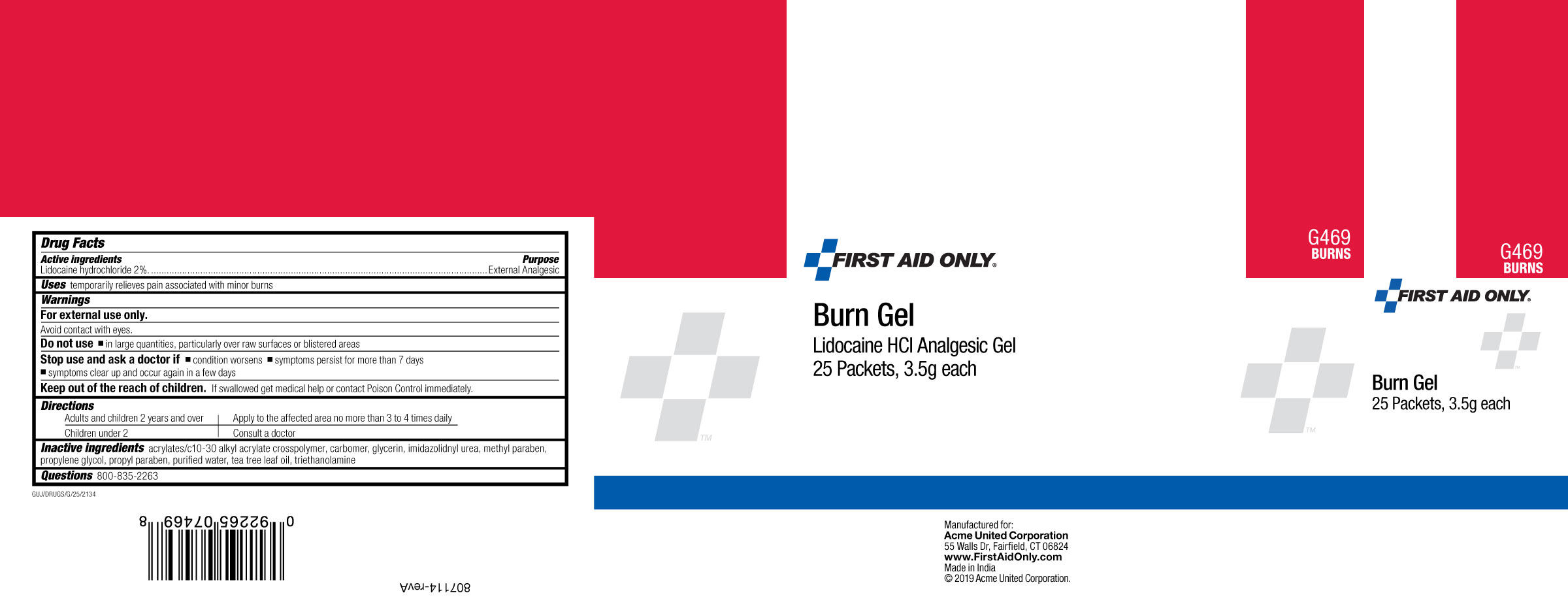 DRUG LABEL: First Aid Only Burn
NDC: 0924-5010 | Form: GEL
Manufacturer: Acme United Corporation
Category: otc | Type: HUMAN OTC DRUG LABEL
Date: 20241117

ACTIVE INGREDIENTS: LIDOCAINE HYDROCHLORIDE 20 mg/1 g
INACTIVE INGREDIENTS: TEA TREE OIL; CARBOMER HOMOPOLYMER TYPE C (ALLYL PENTAERYTHRITOL CROSSLINKED); CARBOMER COPOLYMER TYPE A (ALLYL PENTAERYTHRITOL CROSSLINKED); GLYCERIN; PROPYLENE GLYCOL; IMIDUREA; TROLAMINE; WATER; METHYLPARABEN; PROPYLPARABEN

First Aid Only Burn Gel

• ACTIVE INGREDIENT

Lidocaine Hydrochloride 2%

• PURPOSE

External Analgesic

USES

Temporarily relieves pain associated with minor burns

WARNINGS

For external use only.

Avoid contact with eyes

Do not use

▪ in large quantities, particularly over raw surfaces or blistered areas

Stop use and ask a doctor if

▪condition worsens

▪symptoms persist for more than 7 days

▪symptoms clear up and occur again in a few days

Keep out of reach of children.

. If swallowed get medical help or contact Poison Control immediately

DIRECTIONS

Adults and children 2 years and over:

Adults and children 2 years of age and older: apply to affected area not more than 3 to 4 times daily.

Children under 2 years of age: consult a doctor

INACTIVE INGREDIENTS

Acrylates/C10-30 alkyl acrylate crosspolymer, Carbomer, Glycerin, Imidazolidinyl urea, Methylparaben, Propylparaben, Propylene Glycol, Purified water, Tea Tree Leaf Oil, Triethanolamine.

QUESTIONS 800-835-2263